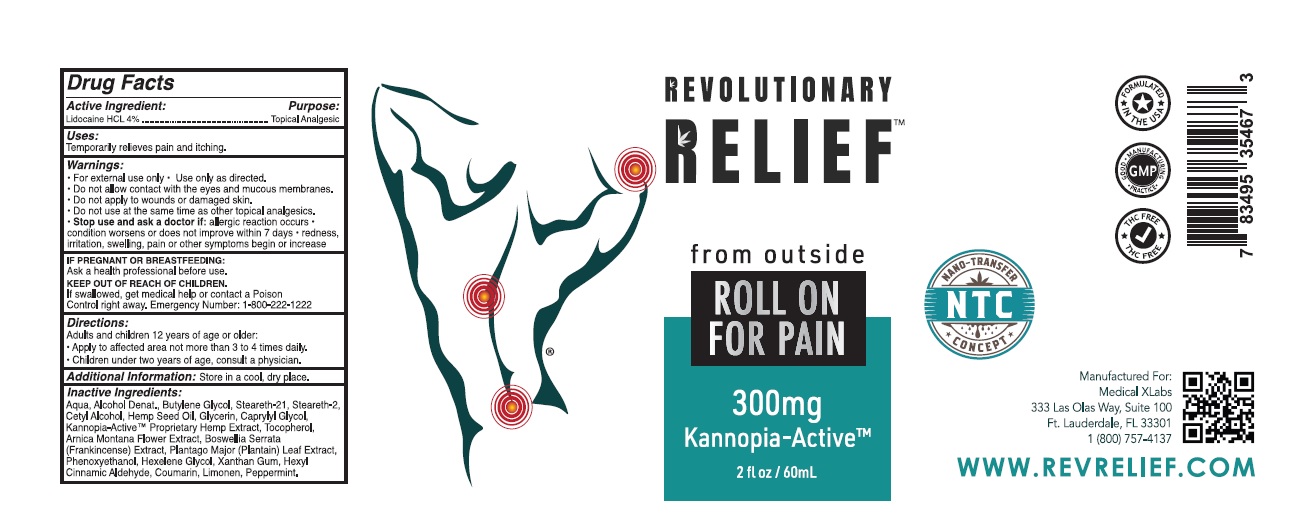 DRUG LABEL: RR Roll-On for Pain
NDC: 83048-001 | Form: GEL
Manufacturer: Revolutionary Relief dba Medical XLabs
Category: otc | Type: HUMAN OTC DRUG LABEL
Date: 20241126

ACTIVE INGREDIENTS: LIDOCAINE HYDROCHLORIDE 4 g/100 mL
INACTIVE INGREDIENTS: WATER; ALCOHOL; BUTYLENE GLYCOL; STEARETH-21; STEARETH-2; CETYL ALCOHOL; CANNABIS SATIVA SEED OIL; GLYCERIN; CAPRYLYL GLYCOL; HEMP; TOCOPHEROL; ARNICA MONTANA FLOWER; INDIAN FRANKINCENSE; PLANTAGO MAJOR LEAF; PHENOXYETHANOL; HEXYLENE GLYCOL; XANTHAN GUM; .ALPHA.-HEXYLCINNAMALDEHYDE; COUMARIN; LIMONENE, (+)-; PEPPERMINT

Active Ingredient

Lidocaine HCL 4%

Purpose

Topical Analgesic

Uses

Temporarily relieves pain and itching

Warnings

- For external use only Use only as direacted
- Do not allow contact with the eyes and mucuous membrances.
- Do not apply to wounds or damaged skin
- Do not use at the same time as other topical analgesics
- Stop use and ask a doctor if: allergic reaction occurs
- condition worsen or does not improve within 7 days
- redness, irritation, swelling, pain or other symptoms begin or increase.
- If pregnant or Breastfeeding

Ask a health professional before use.

Keep out of reach of children

If swallowed, get medical help or Contact a Posion Control right away. Emergency number : 1-800-222-1222

Direaction

Adults and children 12 years of age or older:

- Apply to affected area not more than 3 to 4 times daily
- Children under two years of age, consult a physicion

Additional information

Store in a cool, dry place

Inactive ingredients

Aqua, Alcohol Denat., Butylene Glycol, Steareth-21, Steareth-2, Cetyl Alcohol, Hemp Seed Oil, Glycerin, Caprylyl Glycol, Kannopia-Active TM Proprietary Hemp Extract, Tocopherol, Arnica Montana Flower Extract, Boswellia Serrata (Frankincense) Extract, Plantago Major (Plantain) Leaf
Extract, Phenoxyethanol, Hexelene Glycol, Xanthan Gum, Hexyl Cinnamic Aldehyde, Coumarin, Limonene, Peppermint